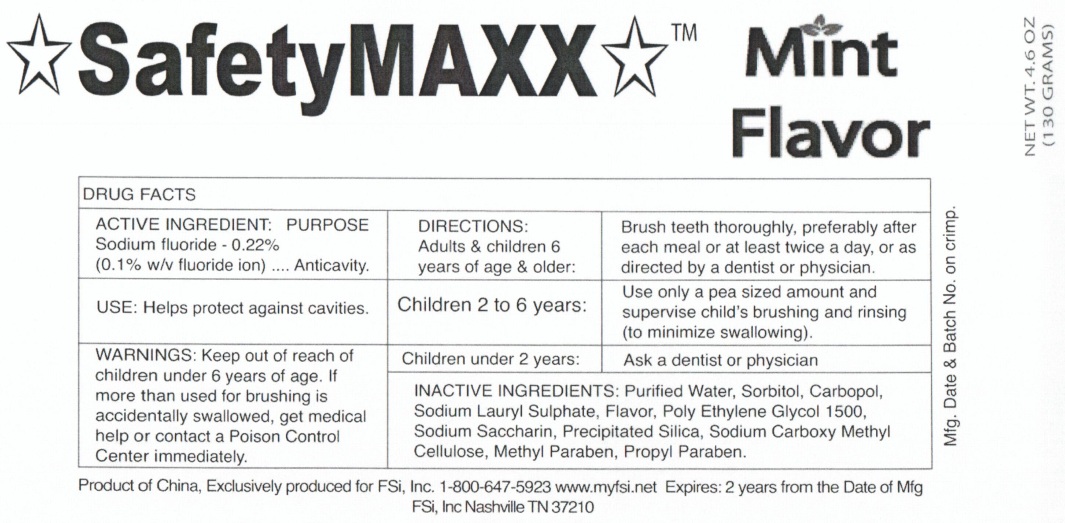 DRUG LABEL: SafetyMAXX Mint Flavor
NDC: 60371-344 | Form: GEL, DENTIFRICE
Manufacturer: FSi, Inc.
Category: otc | Type: HUMAN OTC DRUG LABEL
Date: 20111115

ACTIVE INGREDIENTS: SODIUM FLUORIDE 0.22 g/100 g
INACTIVE INGREDIENTS: WATER; SORBITOL; SODIUM LAURYL SULFATE; POLYETHYLENE GLYCOL 1500; SACCHARIN SODIUM DIHYDRATE; CARBOXYMETHYLCELLULOSE SODIUM; METHYLPARABEN; PROPYLPARABEN

SafetyMAXX Mint Flavor

Active Ingredient

Sodium Fluoride - 0.22% (0.1%w/v fluoride ion)

Purpose

Anticavity

Use:

Helps protect against cavities

Warnings

If more than used for brushing is swallowed, get medical help or contact a Poison Control Center immediately.

Keep out of reach of children under 6years of age.

Directions

Adults and children 6 years of age and older: Brush teeth thoroughly, preferably after each meal or at least twice a day, or as directed by a dentist.

Children 2 to 6 years: Use only a pea sized amount and supervise child's brushing and rinsing (to minimize swallowing)
Children under 2 years: ask a dentist or physician

Inactive Ingredients

Purified water, Sorbitol, Carbopol, Sodium Lauryl Sulphate, Flavor, Poly Ethylene Glycol 1500, Sodium Saccharin, Precipitated Silica, Sodium Carboxy Methyl Cellulose, Methyl Paraben, Propyl Paraben

Product of China, Exclusively produced for FSi, Inc. 1-800-647-5923 www.myfsi.net Expires 2 years from the DAte of Mfg

FSi, Inc Nashville TN 37210